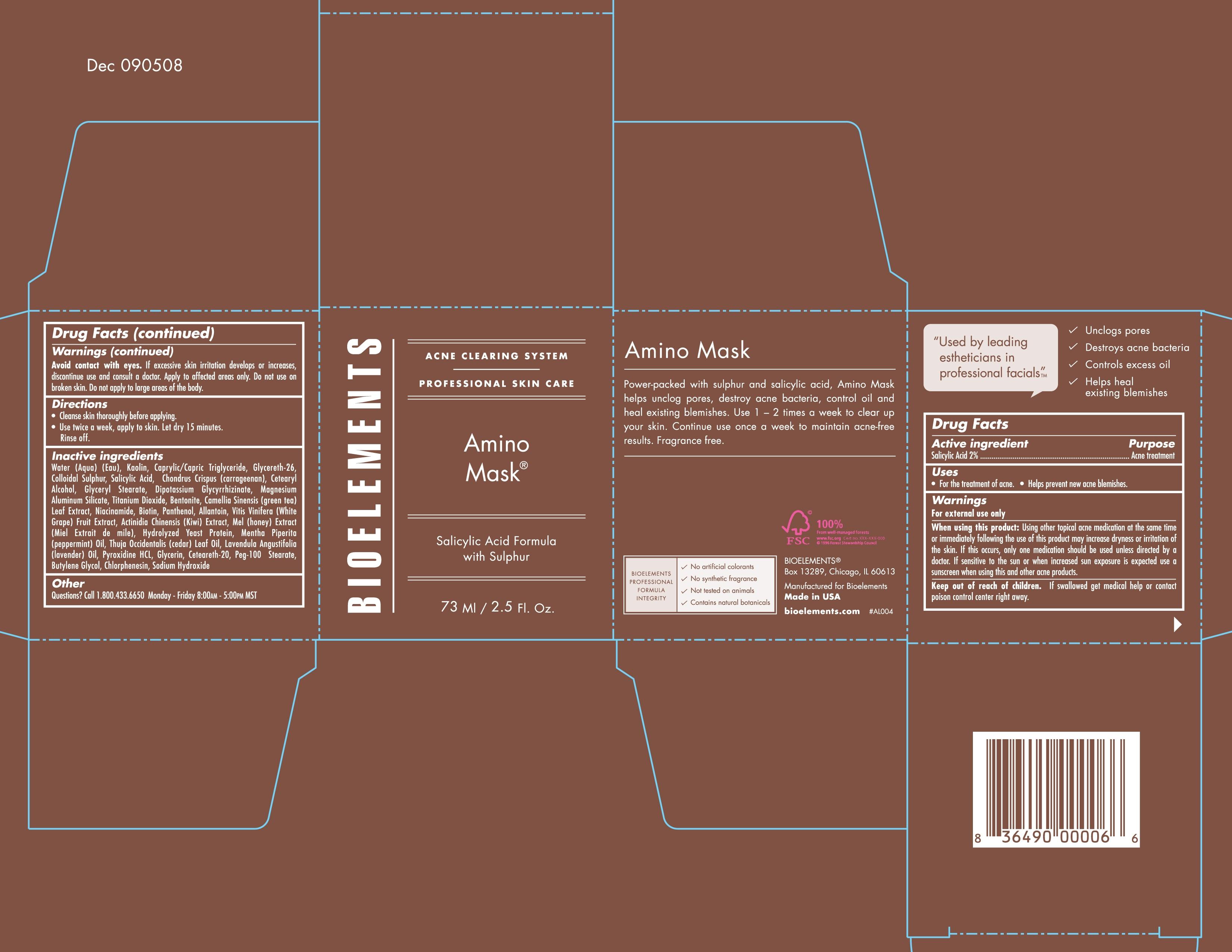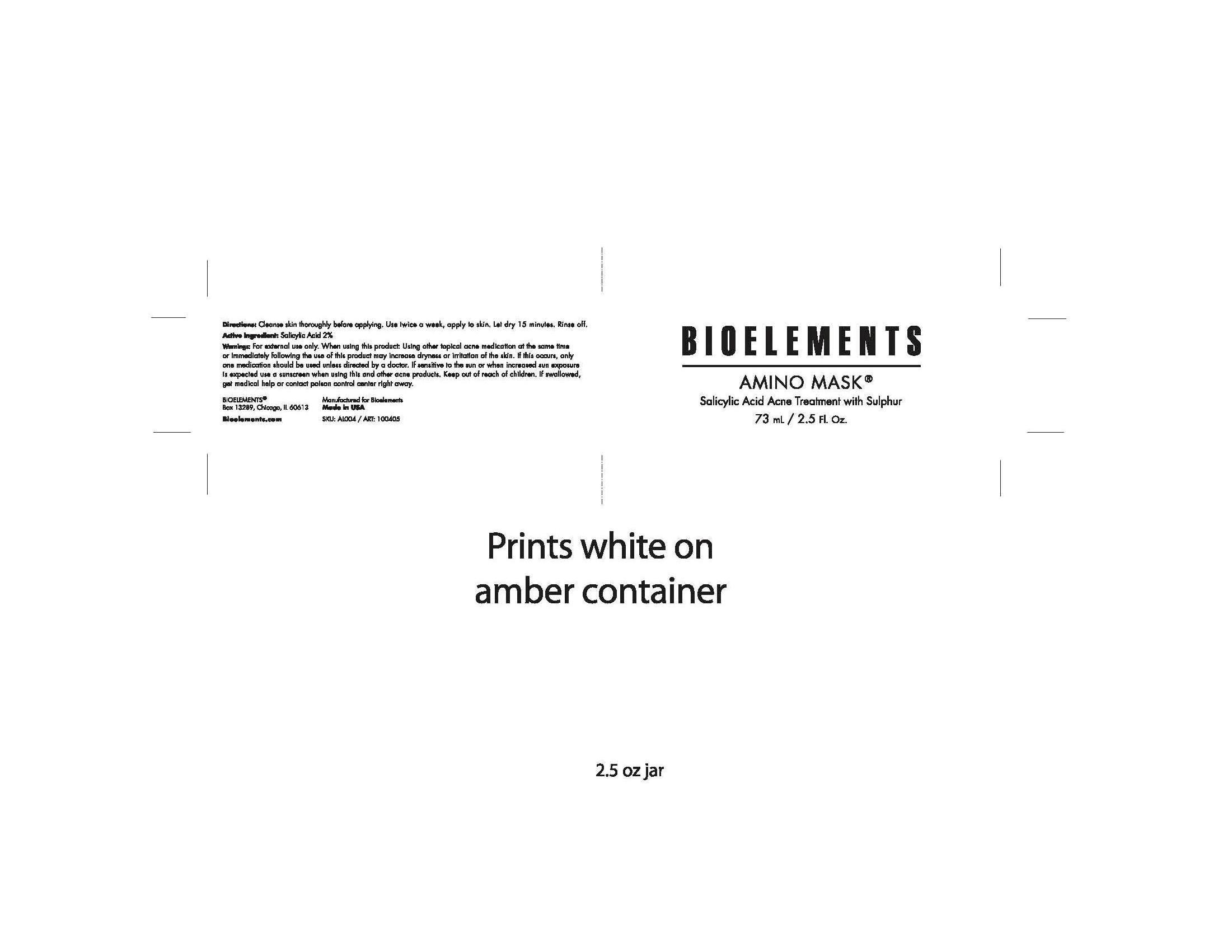 DRUG LABEL: Bioelements
NDC: 49825-112 | Form: CREAM
Manufacturer: Bioelements
Category: otc | Type: HUMAN OTC DRUG LABEL
Date: 20120322

ACTIVE INGREDIENTS: SALICYLIC ACID 2 mL/100 mL
INACTIVE INGREDIENTS: KAOLIN; MEDIUM-CHAIN TRIGLYCERIDES; GLYCERETH-26; SALICYLIC ACID; CHONDRUS CRISPUS; CETOSTEARYL ALCOHOL; GLYCERYL MONOSTEARATE; MAGNESIUM ALUMINUM SILICATE; TITANIUM DIOXIDE; BENTONITE; NIACINAMIDE; BIOTIN; PANTHENOL; ALLANTOIN; ACTINIDIA CHINENSIS SEED; LAVENDER OIL; GLYCERIN; POLYOXYL 20 CETOSTEARYL ETHER; PEG-100 STEARATE; BUTYLENE GLYCOL; SODIUM HYDROXIDE

Amino Mask

Active Ingredients Purpose
Salicylic Acid 2% Acne Treatment

PURPOSE

-For the treatment of acne
-Helps prevent new acne blemishes

-Keep out of reach of children. If swallowed get medical help or contact poison control center right away.

INDICATIONS AND USAGE

-For External use only
-When using this product: using other topical acne medication at the same time or immediately following the use of this product may increase dryness or irritation of the skin. If this occurs, only one medication should be used unless directed by a doctor. If sensitive to the sun or when increased sun exposure is expected use a sunscreen when using this and other acne products.

WARNINGS

-Avoid contact with eyes. If excessive skin irritation develops or increases, discontinue use and consult a doctor. Apply to affected areas only. Do not use on broken skin. Do not apply to large areas of the body.

DOSAGE AND ADMINISTRATION

-Cleanse skin thoroughly before applying
-Use twice a week, apply to skin. Let dry 15 minutes. Rinse Off.

INACTIVE INGREDIENT

Inactive Ingredients: Water (Aqua) (Eau), Kaolin, Caprylic/Capric Triglyceride, Glycereth-26, Colloidal Sulphur, Salicylic Acid, Chondrus Crispus (carrageenan), Cetearyl Alcohol, Glyceryl Stearate, Dipotassium Glycyrrhizinate, Magnesium Aluminum Silicate, Titanium Dioxide, Bentonite, Camellia Sinensis (Green Tea) Leaf Extract, Niacinamide, Biotin, Panthenol, Allantoin, Vitis Vinifera (White Grape) Fruit Extract, Actinidia Chinensis (Kiwi) Extract, Mel (Honey) Extract (Miel Extrait de mile), Hydrolyzed Yeast Protein, Metha Piperita (Peppermint) Oil, Thuja Occidentalis (Cedar) Leaf Oil, Lavandula Angustifolia (Lavender) Oil, Pyroxidine HCL, Glycerin, Ceteareth-20, PEG-100 Stearate, Butylene Glycol, Chlorophensis, Sodium Hydroxide

PACKAGE LABEL

Bioelements
Amino Mask
73 mL / 2.5 Fl. Oz.